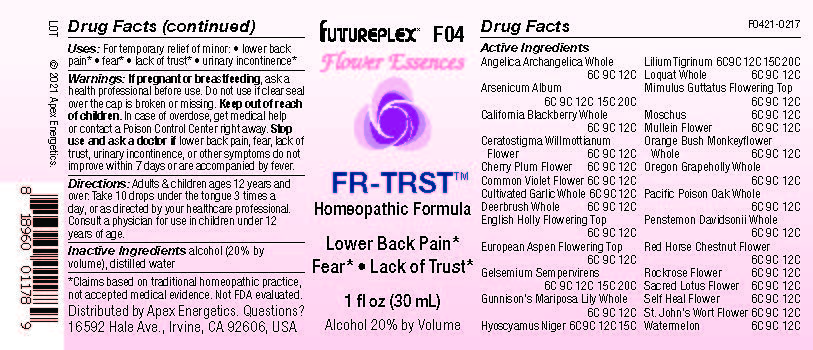 DRUG LABEL: F04
NDC: 63479-0604 | Form: SOLUTION/ DROPS
Manufacturer: Apex Energetics Inc.
Category: homeopathic | Type: HUMAN OTC DRUG LABEL
Date: 20240108

ACTIVE INGREDIENTS: ANGELICA ARCHANGELICA WHOLE 12 [hp_C]/1 mL; ARSENIC TRIOXIDE 20 [kp_C]/1 mL; CERATOSTIGMA WILLMOTTIANUM FLOWER 12 [hp_C]/1 mL; RUBUS URSINUS WHOLE 12 [hp_C]/1 mL; PRUNUS CERASIFERA FLOWER 12 [hp_C]/1 mL; PENSTEMON DAVIDSONII WHOLE 12 [hp_C]/1 mL; HELIANTHEMUM NUMMULARIUM FLOWER 12 [hp_C]/1 mL; NELUMBO NUCIFERA FLOWER 12 [hp_C]/1 mL; HYPERICUM PERFORATUM FLOWER 12 [hp_C]/1 mL; WATERMELON 12 [hp_C]/1 mL; MIMULUS GUTTATUS FLOWERING TOP 12 [hp_C]/1 mL; CEANOTHUS INTEGERRIMUS WHOLE 12 [hp_C]/1 mL; ILEX AQUIFOLIUM FLOWERING TOP 12 [hp_C]/1 mL; HYOSCYAMUS NIGER 15 [hp_C]/1 mL; LILIUM LANCIFOLIUM WHOLE FLOWERING 20 [hp_C]/1 mL; ERIOBOTRYA JAPONICA WHOLE 12 [hp_C]/1 mL; MOSCHUS MOSCHIFERUS MUSK SAC RESIN 12 [hp_C]/1 mL; VERBASCUM DENSIFLORUM FLOWER 12 [hp_C]/1 mL; DIPLACUS AURANTIACUS WHOLE 12 [hp_C]/1 mL; AESCULUS X CARNEA FLOWER 12 [hp_C]/1 mL; PRUNELLA VULGARIS FLOWER 12 [hp_C]/1 mL; TOXICODENDRON DIVERSILOBUM WHOLE 12 [hp_C]/1 mL; VIOLA ODORATA FLOWER 12 [hp_C]/1 mL; ALLIUM SATIVUM WHOLE 12 [hp_C]/1 mL; POPULUS TREMULA FLOWERING TOP 12 [hp_C]/1 mL; GELSEMIUM SEMPERVIRENS ROOT 20 [hp_C]/1 mL; CALOCHORTUS GUNNISONII WHOLE 12 [hp_C]/1 mL; MAHONIA AQUIFOLIUM WHOLE 12 [hp_C]/1 mL
INACTIVE INGREDIENTS: ALCOHOL; WATER

F04

Active Ingredients
Angelica Archangelica Whole | 6C, 9C, 12C
Arsenicum Album | 6C, 9C, 12C 15C 20C
California Blackberry Whole | 6C, 9C, 12C
Ceratostigma Willmottianum Flower | 6C, 9C, 12C
Cherry Plum Flower | 6C, 9C, 12C
Common Violet Flower | 6C, 9C, 12C
Cultivated Garlic Whole | 6C, 9C, 12C
Deerbrush Whole | 6C, 9C, 12C
English Holly Flowering Top | 6C, 9C, 12C
European Aspen Flowering Top | 6C, 9C, 12C
Gelsemium Sempervirens | 6C, 9C, 12C 15C 20C
Gunnison's Mariposa Lily Whole | 6C, 9C, 12C
Hyoscyamus Niger | 6C, 9C, 12C 15C
Lilium Tigrinum | 6C, 9C, 12C 15C 20C
Loquat Whole | 6C, 9C, 12C
Mimulus Guttatus Flowering Top | 6C 9C 12C
Moschus | 6C 9C 12C
Mullein Flower | 6C, 9C, 12C
Orange Bush Monkeyflower Whole | 6C, 9C, 12C
Oregon Grapeholly Whole | 6C, 9C, 12C
Pacific Poisonoak Whole | 6C, 9C, 12C
Penstemon Davidsonii Whole | 6C, 9C, 12C
Red Horse-Chestnut Flower | 6C, 9C, 12C
Rockrose Flower | 6C, 9C, 12C
Sacred Lotus Flower | 6C, 9C, 12C
Self Heal Flower | 6C, 9C, 12C
St. John's Wort Flower | 6C, 9C, 12C
Watermelon | 6C 9C 12C

INDICATIONS AND USAGE

Uses:

For temporary relief of minor:

lower back pain*

fear*

lack of trust*

urinary incontinence*

*Claims based on traditional homeopathic practice, not accepted medical evidence. Not FDA evaluated.

Warnings:

PREGNANCY OR BREAST FEEDING

If pregnant or breastfeeding, ask a health professional before use.

Do not use if clear seal over the cap is broken or missing.

Keep out of reach of children. In case of overdose, get medical help or contact a Poison Control Center right away.

Stop use and ask a doctor if lower back pain, fear, lack of trust, urinary incontinence, or other symptoms do not improve within 7 days or are accompanied by fever.

Directions:

Adults & children ages 12 years and over: Take 10 drops under the tongue 3 times a day, or as directed by your healthcare professional. Consult a physician for use in children under 12 years of age.

Inactive Ingredients

alcohol (20% by volume), distilled water

Distributed by Apex Energetics. Questions?

16592 Hale Ave., Irvine, CA 92606, USA

PACKAGE LABEL

FUTUREPLEX® F04

Flower Essences

FR-TRST™

Homeopathic Formula

Lower Back Pain*

Fear*

Lack of Trust*

1 fl oz (30 mL)

Alcohol 20% by Volume